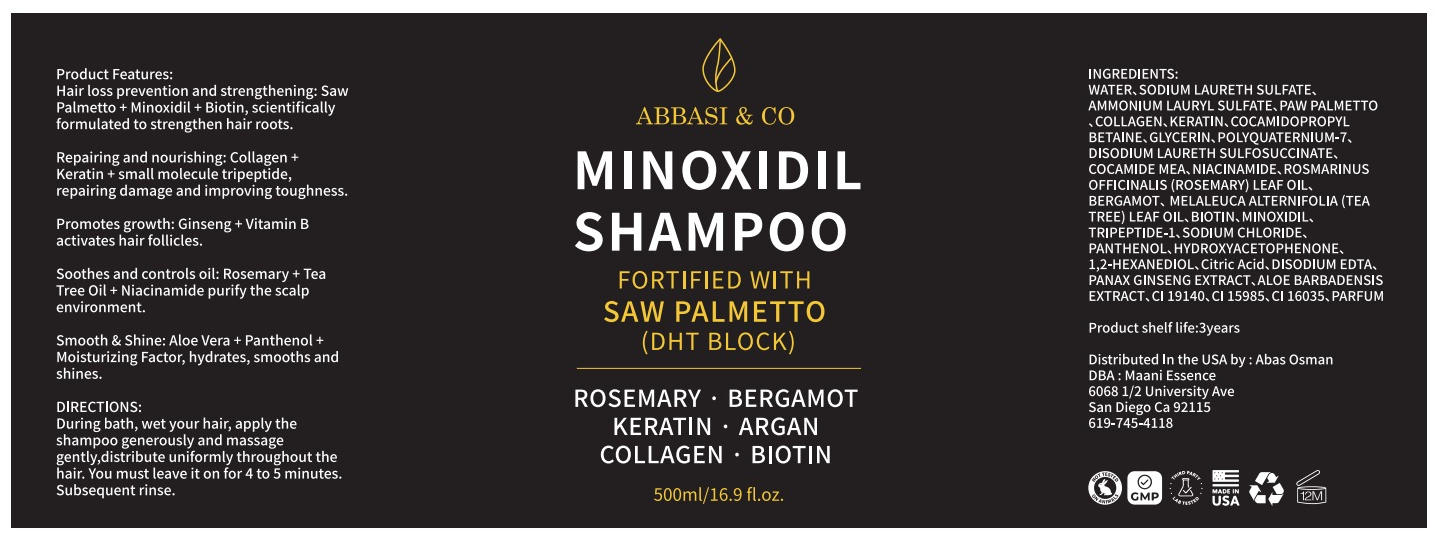 DRUG LABEL: Abbasi and co Minoxidil
NDC: 74458-132 | Form: LIQUID
Manufacturer: Guangzhou Yilong Cosmetics.,Ltd
Category: otc | Type: HUMAN OTC DRUG LABEL
Date: 20260115

ACTIVE INGREDIENTS: MINOXIDIL 5 mg/100 mg
INACTIVE INGREDIENTS: WATER

Abbasi & co Minoxidil shampoo

KEEP OUT OF REACH OF CHILDREN

Eye protection: Avoid getting shampoo foam into your baby's eyes during washing. If it accidentally gets into their eyes, gently rinse with clean water until the irritation subsides. Skin reaction: If persistent redness, itching, or blistering occurs, discontinue use and consult a pediatrician. Storage and handling: Keep out of reach of children, store in a cool, dark place, and avoid direct sunlight and high temperatures. Use within the expiration date indicated on the packaging after opening.

INDICATIONS AND USAGE

Shampoo is used to cleanse the hair and scalp, while also providing a foundation for styling, making hair smooth and nourished, and preventing split ends.

WARNINGS

(I) Shampoo 1. Warning: If it accidentally gets into your eyes, rinse immediately with plenty of water. If irritation persists, seek medical attention. 2. Note: Everyone's hair type is different, and the results may vary. If you experience scalp discomfort or other issues, you may want to switch to a different product. 3. Tip: Use the shampoo correctly according to the instructions. Avoid frequent washing to prevent damage to your scalp and hair.

INACTIVE INGREDIENT

Water

Sodium Laureth Sulfate

Ammonium Lauryl Sulfate

Disodium Laureth Sulfosuccinate

Cocamidopropyl Betaine

Glycerin

Polyquaternium-7

Cocamide MEA

Collagen

Keratin

Niacinamide

Rosmarinus Officinalis (Rosemary) Leaf Oil

Bergamot Oil

Melaleuca Alternifolia (Tea Tree) Leaf Oil

Biotin

Tripeptide-1

Sodium Chloride

Panthenol

Hydroxyacetophenone

1,2-Hexanediol

Citric Acid

Disodium EDTA

Panax Ginseng Extract

Aloe Barbadensis Extract

CI 19140

CI 15985

CI 16035

Parfum

PURPOSE

It cleanses the hair and scalp, removing oil, dirt, dust, and styling product residue, thus maintaining a clean and healthy scalp environment.

These highlights do not include all the information needed to use see full prescribing information for initial U.S. Approver

Apply or spray onto the scalp in the areas of hair loss, not on the hair itself.